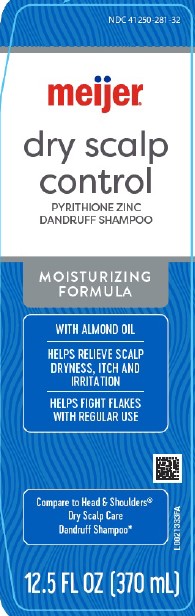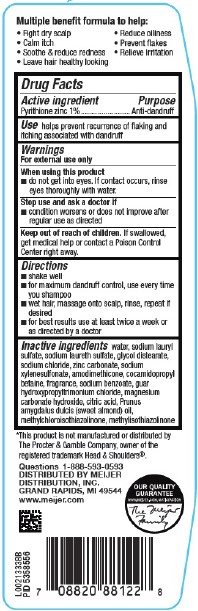 DRUG LABEL: Dandruff
NDC: 41250-281 | Form: SHAMPOO
Manufacturer: Meijer, Inc.
Category: otc | Type: HUMAN OTC DRUG LABEL
Date: 20260219

ACTIVE INGREDIENTS: PYRITHIONE ZINC 10 mg/1 mL
INACTIVE INGREDIENTS: SODIUM XYLENESULFONATE; AMODIMETHICONE (800 CST); COCAMIDOPROPYL BETAINE; SODIUM BENZOATE; GUAR HYDROXYPROPYLTRIMONIUM CHLORIDE (1.7 SUBSTITUENTS PER SACCHARIDE); MAGNESIUM CARBONATE HYDROXIDE; CITRIC ACID MONOHYDRATE; ALMOND OIL; METHYLCHLOROISOTHIAZOLINONE; METHYLISOTHIAZOLINONE; WATER; SODIUM LAURYL SULFATE; SODIUM LAURETH SULFATE; GLYCOL DISTEARATE; SODIUM CHLORIDE; ZINC CARBONATE

Meijer 281.007/284AK-AN
Dandruff Shampoo, Dry Scalp

Claims

Multiple benefit formula to help:

- Fight dry scalp
- Calm itch
- Soothe and reduce redness
- Leave hair healthy looking
- Reduce oiliness
- Prevent flakes
- Relieve irritation

Active ingredient

Pyrithione zinc 1%

Purpose

Anti-dandruff

Use

helps prevent recurrence of flaking and itching associated with dandruff

Warnings

For external use only

When using this product

- do not get into eyes. If contact occurs, rinse eyes thoroughly with water.

Stop use and ask a doctor if

- condition worsens or does not improve after regular use as directed

Keep out of reach of children.

If swallowed, get medical help or contact a Poison Control Center right away.

Directions

- shake well
- for maximum dandruff control, use every time you shampoo
- wet hair, massage onto scalp, rinse, repeat if desired
- for best results use at least twice a week or as directed by a doctor

Inactive ingredients

water, sodium lauryl sulfate, sodium laureth sulfate, glycol distearate, sodium chloride, zinc carbonate, sodium xylenesulfonate, amodimethicone, cocamidopropyl betaine, fragrance, sodium benzoate, guar hydroxypropyltrimonium chloride, magnesium carbonate hydroxide, citric acid, Prunus amygdalus dulcis (sweet almond) oil, methylchloroisothiazolinone, methylisothiazolinone

Disclaimer

*This product is not manufactured or distributed by The Procter & Gamble Company, owner of the registered trademark Head & Shoulders®.

Adverse Reactions

Questions 1-888-593-0593

DISTRIBUTED BY

MEIJER DISTRIBUTION, INC.

GRAND RAPIDS, MI 49544

www.meijer.com

OUR QUALITY GUARANTEE

WWW.MEIJER.COM/SATISFACATION

The Meijer Family

Principal display panel

NDC 41250-281-32

meijer®

dry scalp control

PYRITHIONE ZINC

DANDRUFF SHAMPOO

MOISTURIZING FORMULA

WITH ALMOND OIL

HELPS RELIEVE SCALP DRYNESS, ITCH AND IRRITATION

HELPS FIGHT FLAKES WITH REGULAR USE

Compare to Head & Shoulders®Dry Scalp Care Dandruff Shampoo*

12.5 FL OZ (370 mL)